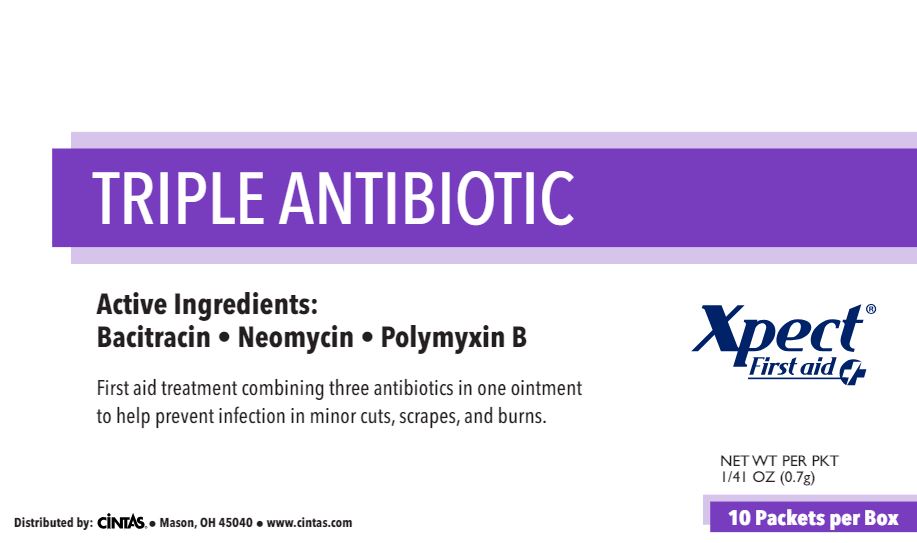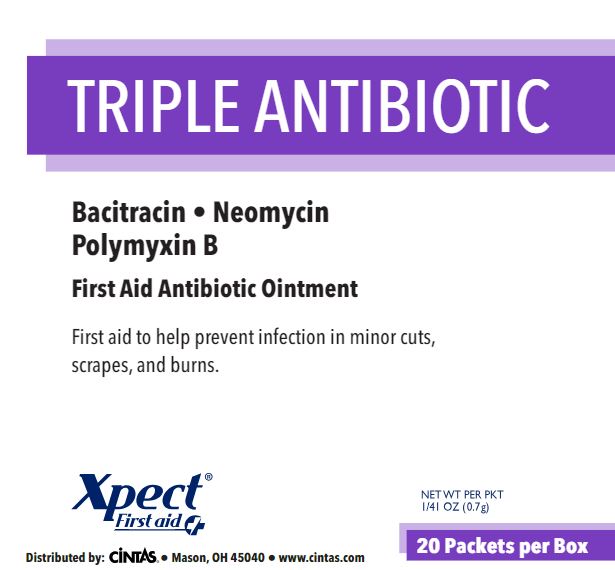 DRUG LABEL: Xpect Triple Antibiotic
NDC: 42961-236 | Form: OINTMENT
Manufacturer: Cintas Corporation
Category: otc | Type: HUMAN OTC DRUG LABEL
Date: 20250926

ACTIVE INGREDIENTS: BACITRACIN ZINC 400 [iU]/1 g; NEOMYCIN SULFATE 3.5 mg/1 g; POLYMYXIN B SULFATE 5000 [iU]/1 g
INACTIVE INGREDIENTS: PETROLATUM

Xpect Triple Antibiotic

Active ingredients (in each gram)

Bacitracin Zinc (400 units Bacitracin)

Neomycin sulfate (3.5 mg Neomycin)

Polymyxin B Sulfate (Polymyxin B 5000 units)

Purpose

First aid antibiotic

First aid antibiotic

First aid antibiotic

Uses

first aid to help prevent infection in

- minor cuts
- scrapes
- burns

Warnings

For external use only

Do not use

- in the eyes
- internally
- over large areas of the body
- longer than 1 week unless directed by a doctor
- if you are allergic to any of the ingredients

Ask a doctor before use

- in case of deep puncture wounds, animal bites, or serious burns

Stop use and ask a doctor if

- the condition persists or gets worse
- a rash or other allergic reaction develops
- condition clears up and occurs again within a few days

Keep out of reach of children. If swallowed, get medical help or contact a Poison Control Center right away.

Directions

- clean the affected area
- apply a small amount of this product (an amount equal to the surface area of the tip of a finger) on the area 1 to 3 times daily
- may be covered with a sterile bandage

Other Information

- store at room temperature (do not freeze)
- do not use packet if opened or torn

Inactive ingredients

petrolatum

Questions or comments?

1-877-973-2811 M-F 8 am - 5 pm

Principal Display Panel 42961-236-02

TRIPLE ANTIBIOTIC

Active Ingredients:

Bacitracin • Neomycin • Polymyxin B

First aid treatment combining three antibiotics in one ointment to help prevent infection in minor cuts, scrapes, and burns.

Distributed by: Cintas® • Mason, OH 45040 • www.cintas.com

Xpect® First aid

NET WT PER PKT 1/41 OZ (0.7g)

10 Packets per Box

Principal Display Panel 42961-236-03

TRIPLE ANTIBIOTIC

Bacitracin • Neomycin • Polymyxin B

First Aid Antibiotic Ointment

First aid to help prevent infection in minor cuts, scrapes, and burns.

Xpect® First aid

Distributed by: Cintas® • Mason, OH 45040 • www.cintas.com

NET WT PER PKT 1/41 OZ (0.7g)

20 Packets per Box